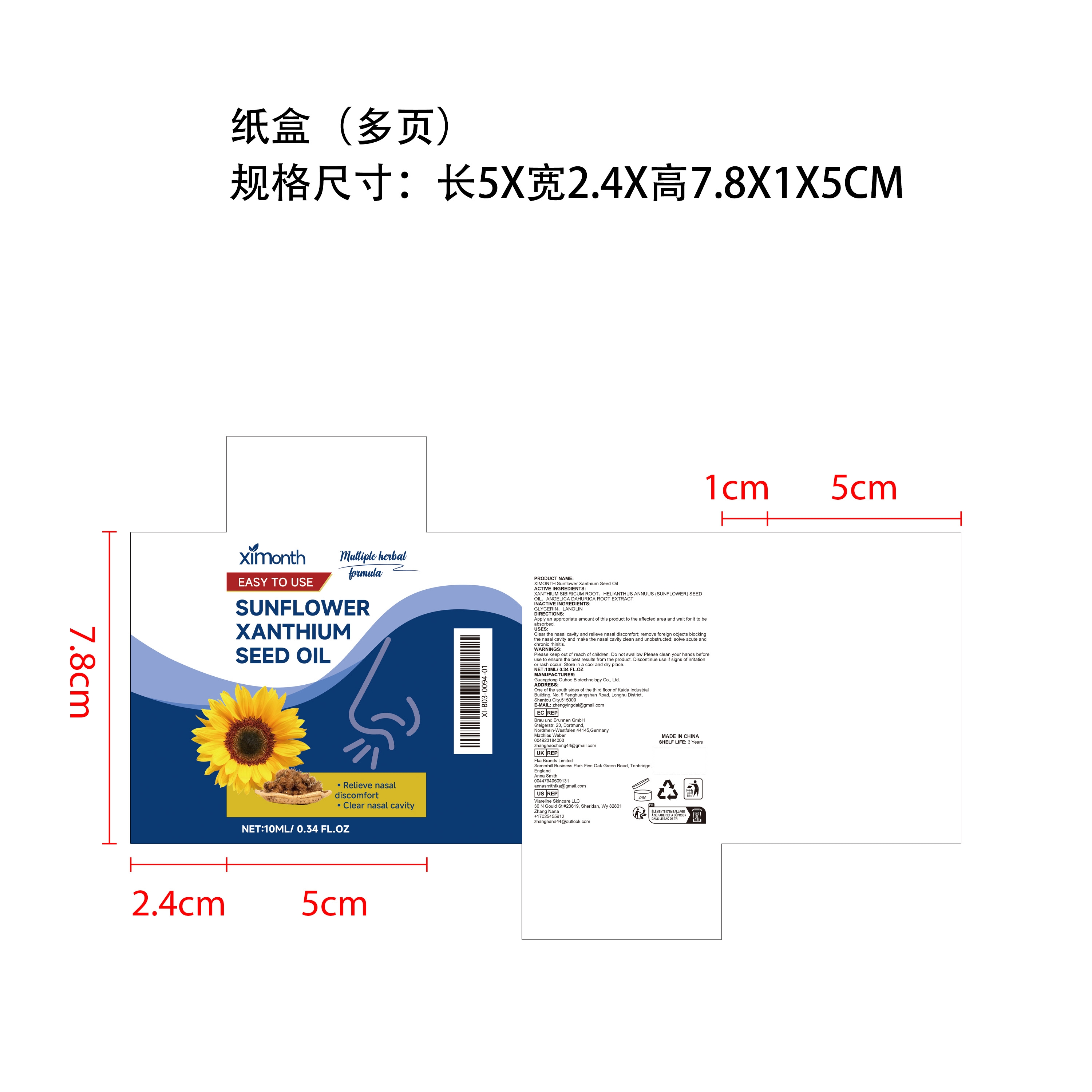 DRUG LABEL: XIMONTH Sunflower Xanthium Seed Oil
NDC: 84744-052 | Form: OIL
Manufacturer: Guangdong Ouhoe Biotechnology Co., Ltd.
Category: otc | Type: HUMAN OTC DRUG LABEL
Date: 20241022

ACTIVE INGREDIENTS: XANTHIUM SIBIRICUM ROOT 3 mg/10 mg; SUNFLOWER OIL 1 mg/10 mg; ANGELICA DAHURICA ROOT 1.5 mg/10 mg
INACTIVE INGREDIENTS: LANOLIN 3 mg/10 mg; GLYCERIN 1.5 mg/10 mg

ACTIVE INGREDIENTS

XANTHIUM SIBIRICUM ROOT,HELIANTHUS ANNUUS (SUNFLOWER) SEED OIL,ANGELICA DAHURICA ROOT EXTRACT

purpose

Clear the nasal cavity and relieve nasal discomfort; remove foreign objects blocking the nasal cavity and make the nasal cavity clean and unobstructed; solve acute and chronic rhinitis.

use

Apply an appropriate amount of this product to the affected area and wait for it to be absorbed.

WARNINGS

Please keep out of reach of children. Do not swallow.Please clean your hands before use to ensure the best results from the product. Discontinue use if signs of irritation or rash occur. Store in a cool and dry place.

Do not use

Discontinue use if signs of irritation or rash occur.

Stop use

Discontinue use if signs of irritation or rash occur.

KEEP OUT OF REACH OF CHILDREN

Please keep out of reach of children. Do not swallow.

STORAGE AND HANDLING

Store in a cool and dry place.

INACTIVE INGREDIENT

GLYCERIN,LANOLIN